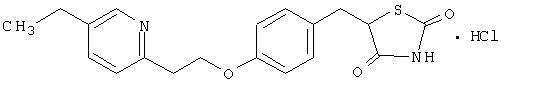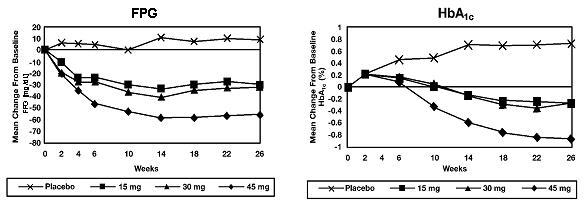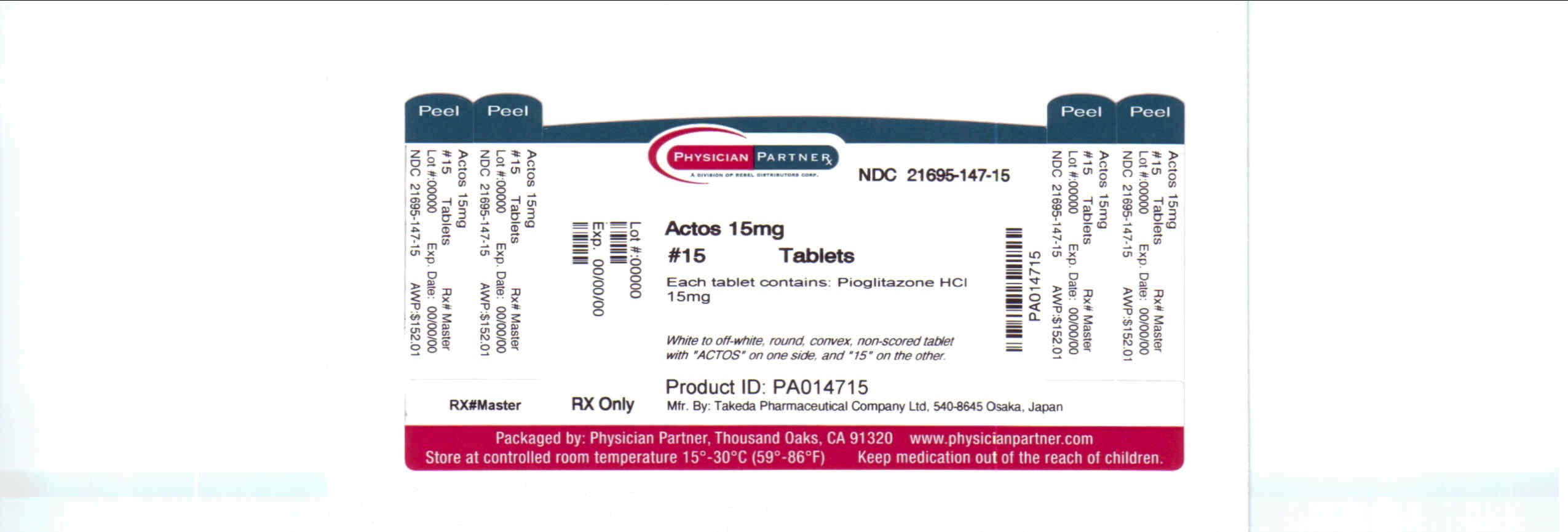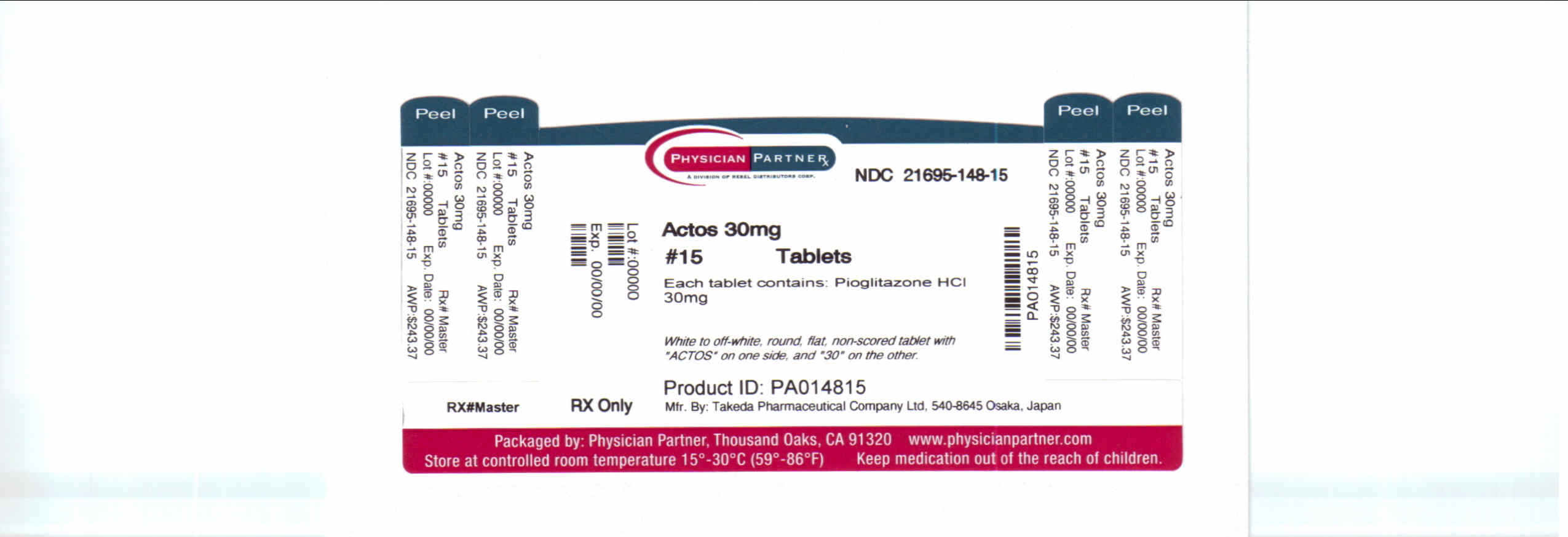 DRUG LABEL: Actos
NDC: 21695-147 | Form: TABLET
Manufacturer: Rebel Distributors Corp.
Category: prescription | Type: HUMAN PRESCRIPTION DRUG LABEL
Date: 20100901

ACTIVE INGREDIENTS: pioglitazone hydrochloride 15 mg/1 1

ACTOS®
(pioglitazone hydrochloride) Tablets

WARNING: CONGESTIVE HEART FAILURE

- Thiazolidinediones, including ACTOS, cause or exacerbate congestive heart failure in some patients (see WARNINGS). After initiation of ACTOS, and after dose increases, observe patients carefully for signs and symptoms of heart failure (including excessive, rapid weight gain, dyspnea, and/or edema). If these signs and symptoms develop, the heart failure should be managed according to the current standards of care. Furthermore, discontinuation or dose reduction of ACTOS must be considered.
- ACTOS is not recommended in patients with symptomatic heart failure. Initiation of ACTOS in patients with established NYHA Class III or IV heart failure is contraindicated (see CONTRAINDICATIONS and WARNINGS).

DESCRIPTION

ACTOS (pioglitazone hydrochloride) is an oral antidiabetic agent that acts primarily by decreasing insulin resistance. ACTOS is used in the management of type 2 diabetes mellitus (also known as non-insulin-dependent diabetes mellitus [NIDDM] or adult-onset diabetes). Pharmacological studies indicate that ACTOS improves sensitivity to insulin in muscle and adipose tissue and inhibits hepatic gluconeogenesis. ACTOS improves glycemic control while reducing circulating insulin levels.

Pioglitazone [(±)-5-[[4-[2-(5-ethyl-2-pyridinyl)ethoxy]phenyl]methyl]-2,4-] thiazolidinedione monohydrochloride belongs to a different chemical class and has a different pharmacological action than the sulfonylureas, metformin, or the α-glucosidase inhibitors. The molecule contains one asymmetric carbon, and the compound is synthesized and used as the racemic mixture. The two enantiomers of pioglitazone interconvert in vivo. No differences were found in the pharmacologic activity between the two enantiomers. The structural formula is as shown:

Pioglitazone hydrochloride is an odorless white crystalline powder that has a molecular formula of C19H20N2O3S•HCl and a molecular weight of 392.90 daltons. It is soluble in N,N-dimethylformamide, slightly soluble in anhydrous ethanol, very slightly soluble in acetone and acetonitrile, practically insoluble in water, and insoluble in ether.

ACTOS is available as a tablet for oral administration containing 15 mg, 30 mg, or 45 mg of pioglitazone (as the base) formulated with the following excipients: lactose monohydrate NF, hydroxypropylcellulose NF, carboxymethylcellulose calcium NF, and magnesium stearate NF.

CLINICAL PHARMACOLOGY

Mechanism of Action

ACTOS is a thiazolidinedione antidiabetic agent that depends on the presence of insulin for its mechanism of action. ACTOS decreases insulin resistance in the periphery and in the liver resulting in increased insulin-dependent glucose disposal and decreased hepatic glucose output. Unlike sulfonylureas, pioglitazone is not an insulin secretagogue. Pioglitazone is a potent agonist for peroxisome proliferator-activated receptor-gamma (PPARγ). PPAR receptors are found in tissues important for insulin action such as adipose tissue, skeletal muscle, and liver. Activation of PPARγ nuclear receptors modulates the transcription of a number of insulin responsive genes involved in the control of glucose and lipid metabolism.

In animal models of diabetes, pioglitazone reduces the hyperglycemia, hyperinsulinemia, and hypertriglyceridemia characteristic of insulin-resistant states such as type 2 diabetes. The metabolic changes produced by pioglitazone result in increased responsiveness of insulin-dependent tissues and are observed in numerous animal models of insulin resistance.

Since pioglitazone enhances the effects of circulating insulin (by decreasing insulin resistance), it does not lower blood glucose in animal models that lack endogenous insulin.

Pharmacokinetics and Drug Metabolism

Serum concentrations of total pioglitazone (pioglitazone plus active metabolites) remain elevated 24 hours after once daily dosing. Steady-state serum concentrations of both pioglitazone and total pioglitazone are achieved within 7 days. At steady-state, two of the pharmacologically active metabolites of pioglitazone, Metabolites III (M-III) and IV (M-IV), reach serum concentrations equal to or greater than pioglitazone. In both healthy volunteers and in patients with type 2 diabetes, pioglitazone comprises approximately 30% to 50% of the peak total pioglitazone serum concentrations and 20% to 25% of the total area under the serum concentration-time curve (AUC).

Maximum serum concentration (Cmax), AUC, and trough serum concentrations (Cmin) for both pioglitazone and total pioglitazone increase proportionally at doses of 15 mg and 30 mg per day. There is a slightly less than proportional increase for pioglitazone and total pioglitazone at a dose of 60 mg per day.

Absorption: Following oral administration, in the fasting state, pioglitazone is first measurable in serum within 30 minutes, with peak concentrations observed within 2 hours. Food slightly delays the time to peak serum concentration to 3 to 4 hours, but does not alter the extent of absorption.

Distribution: The mean apparent volume of distribution (Vd/F) of pioglitazone following single-dose administration is 0.63 ± 0.41 (mean ± SD) L/kg of body weight.

Pioglitazone is extensively protein bound (> 99%) in human serum, principally to serum albumin. Pioglitazone also binds to other serum proteins, but with lower affinity. Metabolites M-III and M-IV also are extensively bound (> 98%) to serum albumin.

Metabolism: Pioglitazone is extensively metabolized by hydroxylation and oxidation; the metabolites also partly convert to glucuronide or sulfate conjugates. Metabolites M-II and M-IV (hydroxy derivatives of pioglitazone) and M-III (keto derivative of pioglitazone) are pharmacologically active in animal models of type 2 diabetes. In addition to pioglitazone, M-III and M-IV are the principal drug-related species found in human serum following multiple dosing. At steady-state, in both healthy volunteers and in patients with type 2 diabetes, pioglitazone comprises approximately 30% to 50% of the total peak serum concentrations and 20% to 25% of the total AUC.

In vitro data demonstrate that multiple CYP isoforms are involved in the metabolism of pioglitazone. The cytochrome P450 isoforms involved are CYP2C8 and, to a lesser degree, CYP3A4 with additional contributions from a variety of other isoforms including the mainly extrahepatic CYP1A1. In vivo studies of pioglitazone in combination with P450 inhibitors and substrates have been performed (see Drug Interactions). Urinary 6ß-hydroxycortisol/cortisol ratios measured in patients treated with ACTOS showed that pioglitazone is not a strong CYP3A4 enzyme inducer.

Excretion and Elimination: Following oral administration, approximately 15% to 30% of the pioglitazone dose is recovered in the urine. Renal elimination of pioglitazone is negligible, and the drug is excreted primarily as metabolites and their conjugates. It is presumed that most of the oral dose is excreted into the bile either unchanged or as metabolites and eliminated in the feces.

The mean serum half-life of pioglitazone and total pioglitazone ranges from 3 to 7 hours and 16 to 24 hours, respectively. Pioglitazone has an apparent clearance, CL/F, calculated to be 5 to 7 L/hr.

Special Populations

Renal Insufficiency: The serum elimination half-life of pioglitazone, M-III, and M-IV remains unchanged in patients with moderate (creatinine clearance 30 to 60 mL/min) to severe (creatinine clearance < 30 mL/min) renal impairment when compared to normal subjects. No dose adjustment in patients with renal dysfunction is recommended (see DOSAGE AND ADMINISTRATION).

Hepatic Insufficiency: Compared with normal controls, subjects with impaired hepatic function (Child-Pugh Grade B/C) have an approximate 45% reduction in pioglitazone and total pioglitazone mean peak concentrations but no change in the mean AUC values.

ACTOS therapy should not be initiated if the patient exhibits clinical evidence of active liver disease or serum transaminase levels (ALT) exceed 2.5 times the upper limit of normal (see PRECAUTIONS, Hepatic Effects).

Elderly: In healthy elderly subjects, peak serum concentrations of pioglitazone and total pioglitazone are not significantly different, but AUC values are slightly higher and the terminal half-life values slightly longer than for younger subjects. These changes were not of a magnitude that would be considered clinically relevant.

Pediatrics: Pharmacokinetic data in the pediatric population are not available.

Gender: The mean Cmax and AUC values were increased 20% to 60% in females. As monotherapy and in combination with sulfonylurea, metformin, or insulin, ACTOS improved glycemic control in both males and females. In controlled clinical trials, hemoglobin A1c (HbA1c) decreases from baseline were generally greater for females than for males (average mean difference in HbA1c 0.5%). Since therapy should be individualized for each patient to achieve glycemic control, no dose adjustment is recommended based on gender alone.

Ethnicity: Pharmacokinetic data among various ethnic groups are not available.

Drug-Drug Interactions

The following drugs were studied in healthy volunteers with a co-administration of ACTOS 45 mg once daily. Listed below are the results:

Oral Contraceptives: Co-administration of ACTOS (45 mg once daily) and an oral contraceptive (1 mg norethindrone plus 0.035 mg ethinyl estradiol once daily) for 21 days, resulted in 11% and 11-14% decrease in ethinyl estradiol AUC (0-24h) and Cmax respectively. There were no significant changes in norethindrone AUC (0-24h) and Cmax. In view of the high variability of ethinyl estradiol pharmacokinetics, the clinical significance of this finding is unknown.

Fexofenadine HCl: Co-administration of ACTOS for 7 days with 60 mg fexofenadine administered orally twice daily resulted in no significant effect on pioglitazone pharmacokinetics. ACTOS had no significant effect on fexofenadine pharmacokinetics.

Glipizide: Co-administration of ACTOS and 5 mg glipizide administered orally once daily for 7 days did not alter the steady-state pharmacokinetics of glipizide.

Digoxin: Co-administration of ACTOS with 0.25 mg digoxin administered orally once daily for 7 days did not alter the steady-state pharmacokinetics of digoxin.

Warfarin: Co-administration of ACTOS for 7 days with warfarin did not alter the steady-state pharmacokinetics of warfarin. ACTOS has no clinically significant effect on prothrombin time when administered to patients receiving chronic warfarin therapy.

Metformin: Co-administration of a single dose of metformin (1000 mg) and ACTOS after 7 days of ACTOS did not alter the pharmacokinetics of the single dose of metformin.

Midazolam: Administration of ACTOS for 15 days followed by a single 7.5 mg dose of midazolam syrup resulted in a 26% reduction in midazolam Cmax and AUC.

Ranitidine HCl: Co-administration of ACTOS for 7 days with ranitidine administered orally twice daily for either 4 or 7 days resulted in no significant effect on pioglitazone pharmacokinetics. ACTOS showed no significant effect on ranitidine pharmacokinetics.

Nifedipine ER: Co-administration of ACTOS for 7 days with 30 mg nifedipine ER administered orally once daily for 4 days to male and female volunteers resulted in least square mean (90% CI) values for unchanged nifedipine of 0.83 (0.73 - 0.95) for Cmax and 0.88 (0.80 - 0.96) for AUC. In view of the high variability of nifedipine pharmacokinetics, the clinical significance of this finding is unknown.

Ketoconazole: Co-administration of ACTOS for 7 days with ketoconazole 200 mg administered twice daily resulted in least square mean (90% CI) values for unchanged pioglitazone of 1.14 (1.06 - 1.23) for Cmax, 1.34 (1.26 - 1.41) for AUC and 1.87 (1.71 - 2.04) for Cmin.

Atorvastatin Calcium: Co-administration of ACTOS for 7 days with atorvastatin calcium (LIPITOR®) 80 mg once daily resulted in least square mean (90% CI) values for unchanged pioglitazone of 0.69 (0.57 - 0.85) for Cmax, 0.76 (0.65 - 0.88) for AUC and 0.96 (0.87 - 1.05) for Cmin. For unchanged atorvastatin the least square mean (90% CI) values were 0.77 (0.66 - 0.90) for Cmax, 0.86 (0.78 - 0.94) for AUC and 0.92 (0.82 - 1.02) for Cmin.

Theophylline: Co-administration of ACTOS for 7 days with theophylline 400 mg administered twice daily resulted in no change in the pharmacokinetics of either drug.

Cytochrome P450: See PRECAUTIONS

Gemfibrozil: Concomitant administration of gemfibrozil (oral 600 mg twice daily), an inhibitor of CYP2C8, with pioglitazone (oral 30 mg) in 10 healthy volunteers pre-treated for 2 days prior with gemfibrozil (oral 600 mg twice daily) resulted in pioglitazone exposure (AUC0-24) being 226% of the pioglitazone exposure in the absence of gemfibrozil (see PRECAUTIONS).^1

Rifampin: Concomitant administration of rifampin (oral 600 mg once daily), an inducer of CYP2C8 with pioglitazone (oral 30 mg) in 10 healthy volunteers pre-treated for 5 days prior with rifampin (oral 600 mg once daily) resulted in a decrease in the AUC of pioglitazone by 54% (see PRECAUTIONS).^2

Pharmacodynamics and Clinical Effects

Clinical studies demonstrate that ACTOS improves insulin sensitivity in insulin-resistant patients. ACTOS enhances cellular responsiveness to insulin, increases insulin-dependent glucose disposal, improves hepatic sensitivity to insulin, and improves dysfunctional glucose homeostasis. In patients with type 2 diabetes, the decreased insulin resistance produced by ACTOS results in lower plasma glucose concentrations, lower plasma insulin levels, and lower HbA1c values. Based on results from an open-label extension study, the glucose lowering effects of ACTOS appear to persist for at least one year. In controlled clinical trials, ACTOS in combination with sulfonylurea, metformin, or insulin had an additive effect on glycemic control.

Patients with lipid abnormalities were included in clinical trials with ACTOS. Overall, patients treated with ACTOS had mean decreases in triglycerides, mean increases in HDL cholesterol, and no consistent mean changes in LDL and total cholesterol.

In a 26-week, placebo-controlled, dose-ranging study, mean triglyceride levels decreased in the 15 mg, 30 mg, and 45 mg ACTOS dose groups compared to a mean increase in the placebo group. Mean HDL levels increased to a greater extent in patients treated with ACTOS than in the placebo-treated patients. There were no consistent differences for LDL and total cholesterol in patients treated with ACTOS compared to placebo (Table 1).

Table 1 Lipids in a 26-Week Placebo-Controlled Monotherapy Dose-Ranging Study
 | Placebo | ACTOS 15 mg Once Daily | ACTOS 30 mg Once Daily | ACTOS 45 mg Once Daily
Triglycerides (mg/dL) | N=79 | N=79 | N=84 | N=77
Baseline (mean) | 262.8 | 283.8 | 261.1 | 259.7
Percent change from baseline (mean) | 4.8% | -9.0% | -9.6% | -9.3%
HDL Cholesterol (mg/dL) | N=79 | N=79 | N=83 | N=77
Baseline (mean) | 41.7 | 40.4 | 40.8 | 40.7
Percent change from baseline (mean) | 8.1% | 14.1% | 12.2% | 19.1%
LDL Cholesterol (mg/dL) | N=65 | N=63 | N=74 | N=62
Baseline (mean) | 138.8 | 131.9 | 135.6 | 126.8
Percent change from baseline (mean) | 4.8% | 7.2% | 5.2% | 6.0%
Total Cholesterol (mg/dL) | N=79 | N=79 | N=84 | N=77
Baseline (mean) | 224.6 | 220.0 | 222.7 | 213.7
Percent change from baseline (mean) | 4.4% | 4.6% | 3.3% | 6.4%

In the two other monotherapy studies (24 weeks and 16 weeks) and in combination therapy studies with sulfonylurea (24 weeks and 16 weeks) and metformin (24 weeks and 16 weeks), the results were generally consistent with the data above. In placebo-controlled trials, the placebo-corrected mean changes from baseline decreased 5% to 26% for triglycerides and increased 6% to 13% for HDL in patients treated with ACTOS. A similar pattern of results was seen in 24-week combination therapy studies of ACTOS with sulfonylurea or metformin.

In a combination therapy study with insulin (16 weeks), the placebo-corrected mean percent change from baseline in triglyceride values for patients treated with ACTOS was also decreased. A placebo-corrected mean change from baseline in LDL cholesterol of 7% was observed for the 15 mg dose group. Similar results to those noted above for HDL and total cholesterol were observed. A similar pattern of results was seen in a 24-week combination therapy study with ACTOS with insulin.

Clinical Studies

Monotherapy

In the U.S., three randomized, double-blind, placebo-controlled trials with durations from 16 to 26 weeks were conducted to evaluate the use of ACTOS as monotherapy in patients with type 2 diabetes. These studies examined ACTOS at doses up to 45 mg or placebo once daily in 865 patients.

In a 26-week, dose-ranging study, 408 patients with type 2 diabetes were randomized to receive 7.5 mg, 15 mg, 30 mg, or 45 mg of ACTOS, or placebo once daily. Therapy with any previous antidiabetic agent was discontinued 8 weeks prior to the double-blind period. Treatment with 15 mg, 30 mg, and 45 mg of ACTOS produced statistically significant improvements in HbA1c and fasting plasma glucose (FPG) at endpoint compared to placebo (Figure 1, Table 2).

Figure 1 shows the time course for changes in FPG and HbA1c for the entire study population in this 26-week study.

BOXED WARNING

Figure 1 Mean Change from Baseline for FPG and HbA1c in a 26-Week Placebo-
Controlled Dose-Ranging Study

Table 2 shows HbA1c and FPG values for the entire study population.

Table 2 Glycemic Parameters in a 26-Week Placebo-Controlled Dose-Ranging Study
 | Placebo | ACTOS 15 mg Once Daily | ACTOS 30 mg Once Daily | ACTOS 45 mg Once Daily
TOTAL POPULATION
HbA 1c (%) | N=79 | N=79 | N=85 | N=76
Baseline (mean) | 10.4 | 10.2 | 10.2 | 10.3
Change from baseline (adjusted mean^+) | 0.7 | -0.3 | -0.3 | -0.9
Difference from placebo (adjusted mean^+) |  | -1.0* | -1.0* | -1.6*
FPG (mg/dL) | N=79 | N=79 | N=84 | N=77
Baseline (mean) | 268 | 267 | 269 | 276
Change from baseline (adjusted mean^+) | 9 | -30 | -32 | -56
Difference from placebo (adjusted mean^+) |  | -39* | -41* | -65*
^+ Adjusted for baseline, pooled center, and pooled center by treatment interaction
* p ≤ 0.050 vs. placebo

The study population included patients not previously treated with antidiabetic medication (naïve; 31%) and patients who were receiving antidiabetic medication at the time of study enrollment (previously treated; 69%). The data for the naïve and previously-treated patient subsets are shown in Table 3. All patients entered an 8 week washout/run-in period prior to double-blind treatment. This run-in period was associated with little change in HbA1c and FPG values from screening to baseline for the naïve patients; however, for the previously-treated group, washout from previous antidiabetic medication resulted in deterioration of glycemic control and increases in HbA1c and FPG. Although most patients in the previously-treated group had a decrease from baseline in HbA1c and FPG with ACTOS, in many cases the values did not return to screening levels by the end of the study. The study design did not permit the evaluation of patients who switched directly to ACTOS from another antidiabetic agent.

Table 3 Glycemic Parameters in a 26-Week Placebo-Controlled Dose-Ranging Study
 | Placebo | ACTOS 15 mg Once Daily | ACTOS 30 mg Once Daily | ACTOS 45 mg Once Daily
Naïve to Therapy HbA 1c (%) | N=25 | N=26 | N=26 | N=21
Screening (mean) | 9.3 | 10.0 | 9.5 | 9.8
Baseline (mean) | 9.0 | 9.9 | 9.3 | 10.0
Change from baseline (adjusted mean*) | 0.6 | -0.8 | -0.6 | -1.9
Difference from placebo (adjusted mean*) |  | -1.4 | -1.3 | -2.6
FPG (mg/dL) | N=25 | N=26 | N=26 | N=21
Screening (mean) | 223 | 245 | 239 | 239
Baseline (mean) | 229 | 251 | 225 | 235
Change from baseline (adjusted mean*) | 16 | -37 | -41 | -64
Difference from placebo (adjusted mean*) |  | -52 | -56 | -80
Previously Treated HbA 1c (%) | N=54 | N=53 | N=59 | N=55
Screening (mean) | 9.3 | 9.0 | 9.1 | 9.0
Baseline (mean) | 10.9 | 10.4 | 10.4 | 10.6
Change from baseline (adjusted mean*) | 0.8 | -0.1 | -0.0 | -0.6
Difference from placebo (adjusted mean*) |  | -1.0 | -0.9 | -1.4
FPG (mg/dL) | N=54 | N=53 | N=58 | N=56
Screening (mean) | 222 | 209 | 230 | 215
Baseline (mean) | 285 | 275 | 286 | 292
Change from baseline (adjusted mean*) | 4 | -32 | -27 | -55
Difference from placebo (adjusted mean*) |  | -36 | -31 | -59
* Adjusted for baseline and pooled center

In a 24-week, placebo-controlled study, 260 patients with type 2 diabetes were randomized to one of two forced-titration ACTOS treatment groups or a mock titration placebo group. Therapy with any previous antidiabetic agent was discontinued 6 weeks prior to the double-blind period. In one ACTOS treatment group, patients received an initial dose of 7.5 mg once daily. After four weeks, the dose was increased to 15 mg once daily and after another four weeks, the dose was increased to 30 mg once daily for the remainder of the study (16 weeks). In the second ACTOS treatment group, patients received an initial dose of 15 mg once daily and were titrated to 30 mg once daily and 45 mg once daily in a similar manner. Treatment with ACTOS, as described, produced statistically significant improvements in HbA1c and FPG at endpoint compared to placebo (Table 4).

Table 4 Glycemic Parameters in a 24-Week Placebo-Controlled Forced-Titration Study
 | Placebo | ACTOS 30 mg^+ Once Daily | ACTOS 45 mg^+ Once Daily
Total Population HbA 1c (%) | N=83 | N=85 | N=85
Baseline (mean) | 10.8 | 10.3 | 10.8
Change from baseline (adjusted mean^++) | 0.9 | -0.6 | -0.6
Difference from placebo (adjusted mean^++) |  | -1.5* | -1.5*
FPG (mg/dL) | N=78 | N=82 | N=85
Baseline (mean) | 279 | 268 | 281
Change from baseline (adjusted mean^++) | 18 | -44 | -50
Difference from placebo (adjusted mean^++) |  | -62* | -68*
^+ Final dose in forced titration
^++ Adjusted for baseline, pooled center, and pooled center by treatment interaction
* p ≤ 0.050 vs. placebo

For patients who had not been previously treated with antidiabetic medication (24%), mean values at screening were 10.1% for HbA1c and 238 mg/dL for FPG. At baseline, mean HbA1c was 10.2% and mean FPG was 243 mg/dL. Compared with placebo, treatment with ACTOS titrated to a final dose of 30 mg and 45 mg resulted in reductions from baseline in mean HbA1c of 2.3% and 2.6% and mean FPG of 63 mg/dL and 95 mg/dL, respectively. For patients who had been previously treated with antidiabetic medication (76%), this medication was discontinued at screening. Mean values at screening were 9.4% for HbA1c and 216 mg/dL for FPG. At baseline, mean HbA1c was 10.7% and mean FPG was 290 mg/dL. Compared with placebo, treatment with ACTOS titrated to a final dose of 30 mg and 45 mg resulted in reductions from baseline in mean HbA1c of 1.3% and 1.4% and mean FPG of 55 mg/dL and 60 mg/dL, respectively. For many previously-treated patients, HbA1c and FPG had not returned to screening levels by the end of the study.

In a 16-week study, 197 patients with type 2 diabetes were randomized to treatment with 30 mg of ACTOS or placebo once daily. Therapy with any previous antidiabetic agent was discontinued 6 weeks prior to the double-blind period. Treatment with 30 mg of ACTOS produced statistically significant improvements in HbA1c and FPG at endpoint compared to placebo (Table 5).

Table 5 Glycemic Parameters in a 16-Week Placebo-Controlled Study
 | Placebo | ACTOS 30 mg Once Daily
Total Population HbA 1c (%) | N=93 | N=100
Baseline (mean) | 10.3 | 10.5
Change from baseline (adjusted mean^+) | 0.8 | -0.6
Difference from placebo (adjusted mean^+) |  | -1.4*
FPG (mg/dL) | N=91 | N=99
Baseline (mean) | 270 | 273
Change from baseline (adjusted mean^+) | 8 | -50
Difference from placebo (adjusted mean^+) |  | -58*
^+ Adjusted for baseline, pooled center, and pooled center by treatment interaction
* p ≤ 0.050 vs. placebo

For patients who had not been previously treated with antidiabetic medication (40%), mean values at screening were 10.3% for HbA1c and 240 mg/dL for FPG. At baseline, mean HbA1c was 10.4% and mean FPG was 254 mg/dL. Compared with placebo, treatment with ACTOS 30 mg resulted in reductions from baseline in mean HbA1c of 1.0% and mean FPG of 62 mg/dL. For patients who had been previously treated with antidiabetic medication (60%), this medication was discontinued at screening. Mean values at screening were 9.4% for HbA1c and 216 mg/dL for FPG. At baseline, mean HbA1c was 10.6% and mean FPG was 287 mg/dL. Compared with placebo, treatment with ACTOS 30 mg resulted in reductions from baseline in mean HbA1c of 1.3% and mean FPG of 46 mg/dL. For many previously-treated patients, HbA1c and FPG had not returned to screening levels by the end of the study.

Combination Therapy

Three 16-week, randomized, double-blind, placebo-controlled clinical studies and three 24-week, randomized, double-blind, dose-controlled clinical studies were conducted to evaluate the effects of ACTOS on glycemic control in patients with type 2 diabetes who were inadequately controlled (HbA1c ≥ 8%) despite current therapy with a sulfonylurea, metformin, or insulin. Previous diabetes treatment may have been monotherapy or combination therapy.

ACTOS Plus Sulfonylurea Studies

Two clinical studies were conducted with ACTOS in combination with a sulfonylurea. Both studies included patients with type 2 diabetes on a sulfonylurea, either alone or in combination with another antidiabetic agent. All other antidiabetic agents were withdrawn prior to starting study treatment. In the first study, 560 patients were randomized to receive 15 mg or 30 mg of ACTOS or placebo once daily for 16 weeks in addition to their current sulfonylurea regimen. When compared to placebo at Week 16, the addition of ACTOS to the sulfonylurea significantly reduced the mean HbA1c by 0.9% and 1.3% and mean FPG by 39 mg/dL and 58 mg/dL for the 15 mg and 30 mg doses, respectively.

In the second study, 702 patients were randomized to receive 30 mg or 45 mg of ACTOS once daily for 24 weeks in addition to their current sulfonylurea regimen. The mean reductions from baseline at Week 24 in HbA1c were 1.55% and 1.67% for the 30 mg and 45 mg doses, respectively. Mean reductions from baseline in FPG were 51.5 mg/dL and 56.1 mg/dL.

The therapeutic effect of ACTOS in combination with sulfonylurea was observed in patients regardless of whether the patients were receiving low, medium, or high doses of sulfonylurea.

ACTOS Plus Metformin Studies

Two clinical studies were conducted with ACTOS in combination with metformin. Both studies included patients with type 2 diabetes on metformin, either alone or in combination with another antidiabetic agent. All other antidiabetic agents were withdrawn prior to starting study treatment. In the first study, 328 patients were randomized to receive either 30 mg of ACTOS or placebo once daily for 16 weeks in addition to their current metformin regimen. When compared to placebo at Week 16, the addition of ACTOS to metformin significantly reduced the mean HbA1c by 0.8% and decreased the mean FPG by 38 mg/dL.

In the second study, 827 patients were randomized to receive either 30 mg or 45 mg of ACTOS once daily for 24 weeks in addition to their current metformin regimen. The mean reductions from baseline at Week 24 in HbA1c were 0.80% and 1.01% for the 30 mg and 45 mg doses, respectively. Mean reductions from baseline in FPG were 38.2 mg/dL and 50.7 mg/dL.

The therapeutic effect of ACTOS in combination with metformin was observed in patients regardless of whether the patients were receiving lower or higher doses of metformin.

ACTOS Plus Insulin Studies

Two clinical studies were conducted with ACTOS in combination with insulin. Both studies included patients with type 2 diabetes on insulin, either alone or in combination with another antidiabetic agent. All other antidiabetic agents were withdrawn prior to starting study treatment. In the first study, 566 patients receiving a median of 60.5 units per day of insulin were randomized to receive either 15 mg or 30 mg of ACTOS or placebo once daily for 16 weeks in addition to their insulin regimen. When compared to placebo at Week 16, the addition of ACTOS to insulin significantly reduced both HbA1c by 0.7% and 1.0% and FPG by 35 mg/dL and 49 mg/dL for the 15 mg and 30 mg dose, respectively.

In the second study, 690 patients receiving a median of 60.0 units per day of insulin received either 30 mg or 45 mg of ACTOS once daily for 24 weeks in addition to their current insulin regimen. The mean reductions from baseline at Week 24 in HbA1c were 1.17% and 1.46% for the 30 mg and 45 mg doses, respectively. Mean reductions from baseline in FPG were 31.9 mg/dL and 45.8 mg/dL. Improved glycemic control was accompanied by mean decreases from baseline in insulin dose requirements of 6.0% and 9.4% per day for the 30 mg and 45 mg dose, respectively.

The therapeutic effect of ACTOS in combination with insulin was observed in patients regardless of whether the patients were receiving lower or higher doses of insulin.

INDICATIONS AND USAGE

ACTOS is indicated as an adjunct to diet and exercise to improve glycemic control in adults with type 2 diabetes mellitus.

CONTRAINDICATIONS

Initiation of ACTOS in patients with established New York Heart Association (NYHA) Class III or IV heart failure is contraindicated (see BOXED WARNING).

ACTOS is contraindicated in patients with known hypersensitivity to this product or any of its components.

WARNINGS

Cardiac Failure and Other Cardiac Effects

ACTOS, like other thiazolidinediones, can cause fluid retention when used alone or in combination with other antidiabetic agents, including insulin. Fluid retention may lead to or exacerbate heart failure. Patients should be observed for signs and symptoms of heart failure. If these signs and symptoms develop, the heart failure should be managed according to current standards of care. Furthermore, discontinuation or dose reduction of ACTOS must be considered (see BOXED WARNING). Patients with NYHA Class III and IV cardiac status were not studied during pre-approval clinical trials and ACTOS is not recommended in these patients (see BOXED WARNING and CONTRAINDICATIONS).

In one 16-week, U.S. double-blind, placebo-controlled clinical trial involving 566 patients with type 2 diabetes, ACTOS at doses of 15 mg and 30 mg in combination with insulin was compared to insulin therapy alone. This trial included patients with long-standing diabetes and a high prevalence of pre-existing medical conditions as follows: arterial hypertension (57.2%), peripheral neuropathy (22.6%), coronary heart disease (19.6%), retinopathy (13.1%), myocardial infarction (8.8%), vascular disease (6.4%), angina pectoris (4.4%), stroke and/or transient ischemic attack (4.1%), and congestive heart failure (2.3%).

In this study, two of the 191 patients receiving 15 mg ACTOS plus insulin (1.1%) and two of the 188 patients receiving 30 mg ACTOS plus insulin (1.1%) developed congestive heart failure compared with none of the 187 patients on insulin therapy alone. All four of these patients had previous histories of cardiovascular conditions including coronary artery disease, previous CABG procedures, and myocardial infarction. In a 24-week, dose-controlled study in which ACTOS was coadministered with insulin, 0.3% of patients (1/345) on 30 mg and 0.9% (3/345) of patients on 45 mg reported CHF as a serious adverse event.

Analysis of data from these studies did not identify specific factors that predict increased risk of congestive heart failure on combination therapy with insulin.

In type 2 diabetes and congestive heart failure (systolic dysfunction)

A 24-week post-marketing safety study was performed to compare ACTOS (n=262) to glyburide (n=256) in uncontrolled diabetic patients (mean HbA1c 8.8% at baseline) with NYHA Class II and III heart failure and ejection fraction less than 40% (mean EF 30% at baseline). Over the course of the study, overnight hospitalization for congestive heart failure was reported in 9.9% of patients on ACTOS compared to 4.7% of patients on glyburide with a treatment difference observed from 6 weeks. This adverse event associated with ACTOS was more marked in patients using insulin at baseline and in patients over 64 years of age. No difference in cardiovascular mortality between the treatment groups was observed.

ACTOS should be initiated at the lowest approved dose if it is prescribed for patients with type 2 diabetes and systolic heart failure (NYHA Class II). If subsequent dose escalation is necessary, the dose should be increased gradually only after several months of treatment with careful monitoring for weight gain, edema, or signs and symptoms of CHF exacerbation.

Prospective Pioglitazone Clinical Trial In Macrovascular Events (PROactive)

In PROactive, 5238 patients with type 2 diabetes and a prior history of macrovascular disease were treated with ACTOS (n=2605), force-titrated up to 45 mg once daily, or placebo (n=2633) (see ADVERSE REACTIONS). The percentage of patients who had an event of serious heart failure was higher for patients treated with ACTOS (5.7%, n=149) than for patients treated with placebo (4.1%, n=108). The incidence of death subsequent to a report of serious heart failure was 1.5% (n=40) in patients treated with ACTOS and 1.4% (n=37) in placebo-treated patients. In patients treated with an insulin-containing regimen at baseline, the incidence of serious heart failure was 6.3% (n=54/864) with ACTOS and 5.2% (n=47/896) with placebo. For those patients treated with a sulfonylurea-containing regimen at baseline, the incidence of serious heart failure was 5.8% (n=94/1624) with ACTOS and 4.4% (n=71/1626) with placebo.

PRECAUTIONS

General

ACTOS exerts its antihyperglycemic effect only in the presence of insulin. Therefore, ACTOS should not be used in patients with type 1 diabetes or for the treatment of diabetic ketoacidosis.

Hypoglycemia: Patients receiving ACTOS in combination with insulin or oral hypoglycemic agents may be at risk for hypoglycemia, and a reduction in the dose of the concomitant agent may be necessary.

Cardiovascular: In U.S. placebo-controlled clinical trials that excluded patients with New York Heart Association (NYHA) Class III and IV cardiac status, the incidence of serious cardiac adverse events related to volume expansion was not increased in patients treated with ACTOS as monotherapy or in combination with sulfonylureas or metformin vs. placebo-treated patients. In insulin combination studies, a small number of patients with a history of previously existing cardiac disease developed congestive heart failure when treated with ACTOS in combination with insulin (see WARNINGS). Patients with NYHA Class III and IV cardiac status were not studied in these ACTOS clinical trials. ACTOS is not indicated in patients with NYHA Class III or IV cardiac status.

In postmarketing experience with ACTOS, cases of congestive heart failure have been reported in patients both with and without previously known heart disease.

Edema: ACTOS should be used with caution in patients with edema. In all U.S. clinical trials, edema was reported more frequently in patients treated with ACTOS than in placebo-treated patients and appears to be dose related (see ADVERSE REACTIONS). In postmarketing experience, reports of initiation or worsening of edema have been received. Since thiazolidinediones, including ACTOS, can cause fluid retention, which can exacerbate or lead to congestive heart failure, ACTOS should be used with caution in patients at risk for heart failure. Patients should be monitored for signs and symptoms of heart failure (see BOXED WARNING, WARNINGS, and PRECAUTIONS, Information for Patients).

Weight Gain: Dose related weight gain was seen with ACTOS alone and in combination with other hypoglycemic agents (Table 6). The mechanism of weight gain is unclear but probably involves a combination of fluid retention and fat accumulation.

Table 6 Weight Changes (kg) from Baseline during Double-Blind Clinical Trials with ACTOS
 |  | Control Group (Placebo) | ACTOS 15 mg | ACTOS 30 mg | ACTOS 45 mg
 |  | Median (25th/75th percentile) | Median (25th/75th percentile) | Median (25th/75th percentile) | Median (25th/75th percentile)
Monotherapy |  | -1.4 (-2.7/0.0) n=256 | 0.9(-0.5/3.4) n = 79 | 1.0(-0.9/3.4) n=188 | 2.6 (0.2/5.4) n = 79
Combination Therapy | Sulfonylurea | -0.5 (-1.8/0.7) n=187 | 2.0 (0.2/3.2) n=183 | 3.1 (1.1/5.4) n=528 | 4.1 (1.8/7.3) n=333
 | Metformin | -1.4 (-3.2/0.3) n=160 | N/A | 0.9(-0.3/3.2) n=567 | 1.8(-0.9/5.0) n=407
 | Insulin | 0.2 (-1.4/1.4) n=182 | 2.3 (0.5/4.3) n=190 | 3.3 (0.9/6.3) n=522 | 4.1 (1.4/6.8) n=338
Note: Trial durations of 16 to 26 weeks

Ovulation: Therapy with ACTOS, like other thiazolidinediones, may result in ovulation in some premenopausal anovulatory women. As a result, these patients may be at an increased risk for pregnancy while taking ACTOS. Thus, adequate contraception in premenopausal women should be recommended. This possible effect has not been investigated in clinical studies so the frequency of this occurrence is not known.

Hematologic: ACTOS may cause decreases in hemoglobin and hematocrit. Across all clinical studies, mean hemoglobin values declined by 2% to 4% in patients treated with ACTOS. These changes primarily occurred within the first 4 to 12 weeks of therapy and remained relatively constant thereafter. These changes may be related to increased plasma volume and have rarely been associated with any significant hematologic clinical effects (see ADVERSE REACTIONS, Laboratory Abnormalities).

Hepatic Effects: In pre-approval clinical studies worldwide, over 4500 subjects were treated with ACTOS. In U.S. clinical studies, over 4700 patients with type 2 diabetes received ACTOS. There was no evidence of drug-induced hepatotoxicity or elevation of ALT levels in the clinical studies.

During pre-approval placebo-controlled clinical trials in the U.S., a total of 4 of 1526 (0.26%) patients treated with ACTOS and 2 of 793 (0.25%) placebo-treated patients had ALT values ≥ 3 times the upper limit of normal. The ALT elevations in patients treated with ACTOS were reversible and were not clearly related to therapy with ACTOS.

In postmarketing experience with ACTOS, reports of hepatitis and of hepatic enzyme elevations to 3 or more times the upper limit of normal have been received. Very rarely, these reports have involved hepatic failure with and without fatal outcome, although causality has not been established.

Pending the availability of the results of additional large, long-term controlled clinical trials and additional postmarketing safety data, it is recommended that patients treated with ACTOS undergo periodic monitoring of liver enzymes.

Serum ALT (alanine aminotransferase) levels should be evaluated prior to the initiation of therapy with ACTOS in all patients and periodically thereafter per the clinical judgment of the health care professional. Liver function tests should also be obtained for patients if symptoms suggestive of hepatic dysfunction occur, e.g., nausea, vomiting, abdominal pain, fatigue, anorexia, or dark urine. The decision whether to continue the patient on therapy with ACTOS should be guided by clinical judgment pending laboratory evaluations. If jaundice is observed, drug therapy should be discontinued.

Therapy with ACTOS should not be initiated if the patient exhibits clinical evidence of active liver disease or the ALT levels exceed 2.5 times the upper limit of normal. Patients with mildly elevated liver enzymes (ALT levels at 1 to 2.5 times the upper limit of normal) at baseline or any time during therapy with ACTOS should be evaluated to determine the cause of the liver enzyme elevation. Initiation or continuation of therapy with ACTOS in patients with mildly elevated liver enzymes should proceed with caution and include appropriate clinical follow-up which may include more frequent liver enzyme monitoring. If serum transaminase levels are increased (ALT > 2.5 times the upper limit of normal), liver function tests should be evaluated more frequently until the levels return to normal or pretreatment values. If ALT levels exceed 3 times the upper limit of normal, the test should be repeated as soon as possible. If ALT levels remain > 3 times the upper limit of normal or if the patient is jaundiced, ACTOS therapy should be discontinued.

Macular Edema: Macular edema has been reported in post-marketing experience in diabetic patients who were taking pioglitazone or another thiazolidinedione. Some patients presented with blurred vision or decreased visual acuity, but some patients appear to have been diagnosed on routine ophthalmologic examination. Some patients had peripheral edema at the time macular edema was diagnosed. Some patients had improvement in their macular edema after discontinuation of their thiazolidinedione. It is unknown whether or not there is a causal relationship between pioglitazone and macular edema. Patients with diabetes should have regular eye exams by an ophthalmologist, per the Standards of Care of the American Diabetes Association. Additionally, any diabetic who reports any kind of visual symptom should be promptly referred to an ophthalmologist, regardless of the patient's underlying medications or other physical findings (see ADVERSE REACTIONS).

Fractures: In a randomized trial (PROactive) in patients with type 2 diabetes (mean duration of diabetes 9.5 years), an increased incidence of bone fracture was noted in female patients taking pioglitazone. During a mean follow-up of 34.5 months, the incidence of bone fracture in females was 5.1% (44/870) for pioglitazone versus 2.5% (23/905) for placebo. This difference was noted after the first year of treatment and remained during the course of the study. The majority of fractures observed in female patients were nonvertebral fractures including lower limb and distal upper limb. No increase in fracture rates was observed in men treated with pioglitazone 1.7% (30/1735) versus placebo 2.1% (37/1728). The risk of fracture should be considered in the care of patients, especially female patients, treated with pioglitazone and attention should be given to assessing and maintaining bone health according to current standards of care.

Macrovascular Outcomes: There have been no clinical studies establishing conclusive evidence of macrovascular risk reduction with ACTOS or any other anti-diabetic drug.

Laboratory Tests

FPG and HbA1c measurements should be performed periodically to monitor glycemic control and the therapeutic response to ACTOS.

Liver enzyme monitoring is recommended prior to initiation of therapy with ACTOS in all patients and periodically thereafter per the clinical judgment of the health care professional (see PRECAUTIONS, General, Hepatic Effects and ADVERSE REACTIONS, Serum Transaminase Levels).

Information for Patients

It is important to instruct patients to adhere to dietary instructions and to have blood glucose and glycosylated hemoglobin tested regularly. During periods of stress such as fever, trauma, infection, or surgery, medication requirements may change and patients should be reminded to seek medical advice promptly.

Patients who experience an unusually rapid increase in weight or edema or who develop shortness of breath or other symptoms of heart failure while on ACTOS should immediately report these symptoms to their physician.

Patients should be told that blood tests for liver function will be performed prior to the start of therapy and periodically thereafter per the clinical judgment of the health care professional. Patients should be told to seek immediate medical advice for unexplained nausea, vomiting, abdominal pain, fatigue, anorexia, or dark urine.

Patients should be told to take ACTOS once daily. ACTOS can be taken with or without meals. If a dose is missed on one day, the dose should not be doubled the following day.

When using combination therapy with insulin or oral hypoglycemic agents, the risks of hypoglycemia, its symptoms and treatment, and conditions that predispose to its development should be explained to patients and their family members.

Therapy with ACTOS, like other thiazolidinediones, may result in ovulation in some premenopausal anovulatory women. As a result, these patients may be at an increased risk for pregnancy while taking ACTOS. Thus, adequate contraception in premenopausal women should be recommended. This possible effect has not been investigated in clinical studies so the frequency of this occurrence is not known.

Drug Interactions

In vivo drug-drug interaction studies have suggested that pioglitazone may be a weak inducer of CYP 450 isoform 3A4 substrate (see CLINICAL PHARMACOLOGY, Metabolism and Drug-Drug Interactions).

An enzyme inhibitor of CYP2C8 (such as gemfibrozil) may significantly increase the AUC of pioglitazone and an enzyme inducer of CYP2C8 (such as rifampin) may significantly decrease the AUC of pioglitazone. Therefore, if an inhibitor or inducer of CYP2C8 is started or stopped during treatment with pioglitazone, changes in diabetes treatment may be needed based on clinical response (see CLINICAL PHARMACOLOGY, Drug-Drug Interactions).

Carcinogenesis, Mutagenesis, Impairment of Fertility

A two-year carcinogenicity study was conducted in male and female rats at oral doses up to 63 mg/kg (approximately 14 times the maximum recommended human oral dose of 45 mg based on mg/m^2). Drug-induced tumors were not observed in any organ except for the urinary bladder. Benign and/or malignant transitional cell neoplasms were observed in male rats at 4 mg/kg/day and above (approximately equal to the maximum recommended human oral dose based on mg/m^2). A two-year carcinogenicity study was conducted in male and female mice at oral doses up to 100 mg/kg/day (approximately 11 times the maximum recommended human oral dose based on mg/m^2). No drug-induced tumors were observed in any organ.

During prospective evaluation of urinary cytology involving more than 1800 patients receiving ACTOS in clinical trials up to one year in duration, no new cases of bladder tumors were identified. In two 3-year studies in which pioglitazone was compared to placebo or glyburide, there were 16/3656 (0.44%) reports of bladder cancer in patients taking pioglitazone compared to 5/3679 (0.14%) in patients not taking pioglitazone. After excluding patients in whom exposure to study drug was less than one year at the time of diagnosis of bladder cancer, there were six (0.16%) cases on pioglitazone and two (0.05%) on placebo.

Pioglitazone HCl was not mutagenic in a battery of genetic toxicology studies, including the Ames bacterial assay, a mammalian cell forward gene mutation assay (CHO/HPRT and AS52/XPRT), an in vitro cytogenetics assay using CHL cells, an unscheduled DNA synthesis assay, and an in vivo micronucleus assay.

No adverse effects upon fertility were observed in male and female rats at oral doses up to 40 mg/kg pioglitazone HCl daily prior to and throughout mating and gestation (approximately 9 times the maximum recommended human oral dose based on mg/m^2).

Animal Toxicology

Heart enlargement has been observed in mice (100 mg/kg), rats (4 mg/kg and above) and dogs (3 mg/kg) treated orally with pioglitazone HCl (approximately 11, 1, and 2 times the maximum recommended human oral dose for mice, rats, and dogs, respectively, based on mg/m^2). In a one-year rat study, drug-related early death due to apparent heart dysfunction occurred at an oral dose of 160 mg/kg/day (approximately 35 times the maximum recommended human oral dose based on mg/m^2). Heart enlargement was seen in a 13-week study in monkeys at oral doses of 8.9 mg/kg and above (approximately 4 times the maximum recommended human oral dose based on mg/m^2), but not in a 52-week study at oral doses up to 32 mg/kg (approximately 13 times the maximum recommended human oral dose based on mg/m^2).

Pregnancy

Pregnancy Category C. Pioglitazone was not teratogenic in rats at oral doses up to 80 mg/kg or in rabbits given up to 160 mg/kg during organogenesis (approximately 17 and 40 times the maximum recommended human oral dose based on mg/m^2, respectively). Delayed parturition and embryotoxicity (as evidenced by increased postimplantation losses, delayed development and reduced fetal weights) were observed in rats at oral doses of 40 mg/kg/day and above (approximately 10 times the maximum recommended human oral dose based on mg/m^2). No functional or behavioral toxicity was observed in offspring of rats. In rabbits, embryotoxicity was observed at an oral dose of 160 mg/kg (approximately 40 times the maximum recommended human oral dose based on mg/m^2). Delayed postnatal development, attributed to decreased body weight, was observed in offspring of rats at oral doses of 10 mg/kg and above during late gestation and lactation periods (approximately 2 times the maximum recommended human oral dose based on mg/m^2).

There are no adequate and well-controlled studies in pregnant women. ACTOS should be used during pregnancy only if the potential benefit justifies the potential risk to the fetus.

Because current information strongly suggests that abnormal blood glucose levels during pregnancy are associated with a higher incidence of congenital anomalies, as well as increased neonatal morbidity and mortality, most experts recommend that insulin be used during pregnancy to maintain blood glucose levels as close to normal as possible.

Nursing Mothers

Pioglitazone is secreted in the milk of lactating rats. It is not known whether ACTOS is secreted in human milk. Because many drugs are excreted in human milk, ACTOS should not be administered to a breastfeeding woman.

Pediatric Use

Safety and effectiveness of ACTOS in pediatric patients have not been established.

Elderly Use

Approximately 500 patients in placebo-controlled clinical trials of ACTOS were 65 and over. No significant differences in effectiveness and safety were observed between these patients and younger patients.

ADVERSE REACTIONS

Over 8500 patients with type 2 diabetes have been treated with ACTOS in randomized, double-blind, controlled clinical trials. This includes 2605 high-risk patients with type 2 diabetes treated with ACTOS from the PROactive clinical trial. Over 6000 patients have been treated for 6 months or longer, and over 4500 patients for one year or longer. Over 3000 patients have received ACTOS for at least 2 years.

The overall incidence and types of adverse events reported in placebo-controlled clinical trials of ACTOS monotherapy at doses of 7.5 mg, 15 mg, 30 mg, or 45 mg once daily are shown in Table 7.

Table 7 Placebo-Controlled Clinical Studies of ACTOS Monotherapy: Adverse Events Reported at a Frequency ≥ 5% of Patients Treated with ACTOS
(% of Patients)
 | Placebo N=259 | ACTOS N=606
Upper Respiratory Tract Infection | 8.5 | 13.2
Headache | 6.9 | 9.1
Sinusitis | 4.6 | 6.3
Myalgia | 2.7 | 5.4
Tooth Disorder | 2.3 | 5.3
Diabetes Mellitus Aggravated | 8.1 | 5.1
Pharyngitis | 0.8 | 5.1

For most clinical adverse events the incidence was similar for groups treated with ACTOS monotherapy and those treated in combination with sulfonylureas, metformin, and insulin. There was an increase in the occurrence of edema in the patients treated with ACTOS and insulin compared to insulin alone.

In a 16-week, placebo-controlled ACTOS plus insulin trial (n=379), 10 patients treated with ACTOS plus insulin developed dyspnea and also, at some point during their therapy, developed either weight change or edema. Seven of these 10 patients received diuretics to treat these symptoms. This was not reported in the insulin plus placebo group.

The incidence of withdrawals from placebo-controlled clinical trials due to an adverse event other than hyperglycemia was similar for patients treated with placebo (2.8%) or ACTOS (3.3%).

In controlled combination therapy studies with either a sulfonylurea or insulin, mild to moderate hypoglycemia, which appears to be dose related, was reported (see PRECAUTIONS, General, Hypoglycemia and DOSAGE and ADMINISTRATION, Combination Therapy).

In U.S. double-blind studies, anemia was reported in ≤ 2% of patients treated with ACTOS plus sulfonylurea, metformin or insulin (see PRECAUTIONS, General, Hematologic).

In monotherapy studies, edema was reported for 4.8% (with doses from 7.5 mg to 45 mg) of patients treated with ACTOS versus 1.2% of placebo-treated patients. In combination therapy studies, edema was reported for 7.2% of patients treated with ACTOS and sulfonylureas compared to 2.1% of patients on sulfonylureas alone. In combination therapy studies with metformin, edema was reported in 6.0% of patients on combination therapy compared to 2.5% of patients on metformin alone. In combination therapy studies with insulin, edema was reported in 15.3% of patients on combination therapy compared to 7.0% of patients on insulin alone. Most of these events were considered mild or moderate in intensity (see PRECAUTIONS, General, Edema).

In one 16-week clinical trial of insulin plus ACTOS combination therapy, more patients developed congestive heart failure on combination therapy (1.1%) compared to none on insulin alone (see WARNINGS, Cardiac Failure and Other Cardiac Effects).

Prospective Pioglitazone Clinical Trial In Macrovascular Events (PROactive)

In PROactive, 5238 patients with type 2 diabetes and a prior history of macrovascular disease were treated with ACTOS (n=2605), force-titrated up to 45 mg daily or placebo (n=2633) in addition to standard of care. Almost all subjects (95%) were receiving cardiovascular medications (beta blockers, ACE inhibitors, ARBs, calcium channel blockers, nitrates, diuretics, aspirin, statins, fibrates). Patients had a mean age of 61.8 years, mean duration of diabetes 9.5 years, and mean HbA1c 8.1%. Average duration of follow-up was 34.5 months. The primary objective of this trial was to examine the effect of ACTOS on mortality and macrovascular morbidity in patients with type 2 diabetes mellitus who were at high risk for macrovascular events. The primary efficacy variable was the time to the first occurrence of any event in the cardiovascular composite endpoint (see table 8 below). Although there was no statistically significant difference between ACTOS and placebo for the 3-year incidence of a first event within this composite, there was no increase in mortality or in total macrovascular events with ACTOS.

Table 8 Number of First and Total Events for Each Component within the Cardiovascular Composite Endpoint
 | Placebo N=2633 |  | ACTOS N=2605
Cardiovascular Events | First Events (N) | Total events (N) | First Events (N) | Total events (N)
Any event | 572 | 900 | 514 | 803
All-cause mortality | 122 | 186 | 110 | 177
Non-fatal MI | 118 | 157 | 105 | 131
Stroke | 96 | 119 | 76 | 92
ACS | 63 | 78 | 42 | 65
Cardiac intervention | 101 | 240 | 101 | 195
Major leg amputation | 15 | 28 | 9 | 28
Leg revascularization | 57 | 92 | 71 | 115

Postmarketing reports of new onset or worsening diabetic macular edema with decreased visual acuity have also been received (see PRECAUTIONS, General, Macular Edema).

Laboratory Abnormalities

Hematologic: ACTOS may cause decreases in hemoglobin and hematocrit. The fall in hemoglobin and hematocrit with ACTOS appears to be dose related. Across all clinical studies, mean hemoglobin values declined by 2% to 4% in patients treated with ACTOS. These changes generally occurred within the first 4 to 12 weeks of therapy and remained relatively stable thereafter. These changes may be related to increased plasma volume associated with ACTOS therapy and have rarely been associated with any significant hematologic clinical effects.

Serum Transaminase Levels: During all clinical studies in the U.S., 14 of 4780 (0.30%) patients treated with ACTOS had ALT values ≥ 3 times the upper limit of normal during treatment. All patients with follow-up values had reversible elevations in ALT. In the population of patients treated with ACTOS, mean values for bilirubin, AST, ALT, alkaline phosphatase, and GGT were decreased at the final visit compared with baseline. Fewer than 0.9% of patients treated with ACTOS were withdrawn from clinical trials in the U.S. due to abnormal liver function tests.

In pre-approval clinical trials, there were no cases of idiosyncratic drug reactions leading to hepatic failure (see PRECAUTIONS, General, Hepatic Effects).

CPK Levels: During required laboratory testing in clinical trials, sporadic, transient elevations in creatine phosphokinase levels (CPK) were observed. An isolated elevation to greater than 10 times the upper limit of normal was noted in 9 patients (values of 2150 to 11400 IU/L). Six of these patients continued to receive ACTOS, two patients had completed receiving study medication at the time of the elevated value and one patient discontinued study medication due to the elevation. These elevations resolved without any apparent clinical sequelae. The relationship of these events to ACTOS therapy is unknown.

OVERDOSAGE

During controlled clinical trials, one case of overdose with ACTOS was reported. A male patient took 120 mg per day for four days, then 180 mg per day for seven days. The patient denied any clinical symptoms during this period.

In the event of overdosage, appropriate supportive treatment should be initiated according to patient’s clinical signs and symptoms.

DOSAGE AND ADMINISTRATION

ACTOS should be taken once daily without regard to meals.

The management of antidiabetic therapy should be individualized. Ideally, the response to therapy should be evaluated using HbA1c which is a better indicator of long-term glycemic control than FPG alone. HbA1c reflects glycemia over the past two to three months. In clinical use, it is recommended that patients be treated with ACTOS for a period of time adequate to evaluate change in HbA1c (three months) unless glycemic control deteriorates. After initiation of ACTOS or with dose increase, patients should be carefully monitored for adverse events related to fluid retention (see BOXED WARNING and WARNINGS).

Monotherapy

ACTOS monotherapy in patients not adequately controlled with diet and exercise may be initiated at 15 mg or 30 mg once daily. For patients who respond inadequately to the initial dose of ACTOS, the dose can be increased in increments up to 45 mg once daily. For patients not responding adequately to monotherapy, combination therapy should be considered.

Combination Therapy

Sulfonylureas: ACTOS in combination with a sulfonylurea may be initiated at 15 mg or 30 mg once daily. The current sulfonylurea dose can be continued upon initiation of ACTOS therapy. If patients report hypoglycemia, the dose of the sulfonylurea should be decreased.

Metformin: ACTOS in combination with metformin may be initiated at 15 mg or 30 mg once daily. The current metformin dose can be continued upon initiation of ACTOS therapy. It is unlikely that the dose of metformin will require adjustment due to hypoglycemia during combination therapy with ACTOS.

Insulin: ACTOS in combination with insulin may be initiated at 15 mg or 30 mg once daily. The current insulin dose can be continued upon initiation of ACTOS therapy. In patients receiving ACTOS and insulin, the insulin dose can be decreased by 10% to 25% if the patient reports hypoglycemia or if plasma glucose concentrations decrease to less than 100 mg/dL. Further adjustments should be individualized based on glucose-lowering response.

Maximum Recommended Dose

The dose of ACTOS should not exceed 45 mg once daily in monotherapy or in combination with sulfonylurea, metformin, or insulin.

Dose adjustment in patients with renal insufficiency is not recommended (see CLINICAL PHARMACOLOGY, Pharmacokinetics and Drug Metabolism).

Therapy with ACTOS should not be initiated if the patient exhibits clinical evidence of active liver disease or increased serum transaminase levels (ALT greater than 2.5 times the upper limit of normal) at start of therapy (see PRECAUTIONS, General, Hepatic Effects and CLINICAL PHARMACOLOGY, Special Populations, Hepatic Insufficiency). Liver enzyme monitoring is recommended in all patients prior to initiation of therapy with ACTOS and periodically thereafter (see PRECAUTIONS, General, Hepatic Effects).

There are no data on the use of ACTOS in patients under 18 years of age; therefore, use of ACTOS in pediatric patients is not recommended.

No data are available on the use of ACTOS in combination with another thiazolidinedione.

HOW SUPPLIED

ACTOS is available in 15 mg, 30 mg, and 45 mg tablets as follows:

15 mg Tablet: white to off-white, round, convex, non-scored tablet with “ACTOS” on one side, and “15” on the other, available in:

NDC 21695-147-15 Bottles of 15

30 mg Tablet: white to off-white, round, flat, non-scored tablet with “ACTOS” on one side, and “30” on the other, available in:

NDC 21695-148-15 Bottles of 15

STORAGE

Store at 25°C (77°F); excursions permitted to 15-30°C (59-86°F) [see USP Controlled Room Temperature]. Keep container tightly closed, and protect from moisture and humidity.

REFERENCES

1. Deng, LJ, et al. Effect of gemfibrozil on the pharmacokinetics of pioglitazone. Eur J Clin Pharmacol 2005; 61: 831-836, Table 1.
2. Jaakkola, T, et al. Effect of rifampicin on the pharmacokinetics of pioglitazone. Clin Pharmacol Brit Jour 2006; 61:1 70-78.

Rx only

Manufactured by:
Takeda Pharmaceutical Company Limited
Osaka, Japan

Marketed by:
Takeda Pharmaceuticals America, Inc.
One Takeda Parkway
Deerfield, IL 60015

Repackaged by:

Rebel Distributors Corp.

Thousand Oaks, CA 91320

ACTOS® is a registered trademark of Takeda Pharmaceutical Company Limited and used under license by Takeda Pharmaceuticals America, Inc.

All other trademark names are the property of their respective owners.

August 2008
ACT0808-R14

MEDICATION GUIDE

ACTOS® (ak-TŌS)
(pioglitazone hydrochloride) tablets

Read this Medication Guide carefully before you start taking ACTOS and each time you get a refill. There may be new information. This information does not take the place of talking with your doctor about your medical condition or your treatment. If you have any questions about ACTOS, ask your doctor or pharmacist.

What is the most important information I should know about ACTOS?

ACTOS can cause serious side effects, including new or worse heart failure.

- ACTOS can cause your body to keep extra fluid (fluid retention), which leads to swelling (edema) and weight gain. Extra body fluid can make some heart problems worse or lead to heart failure. Heart failure means your heart does not pump blood well enough.
- If you have severe heart failure, you cannot start ACTOS.
- If you have heart failure with symptoms (such as shortness of breath or swelling), even if these symptoms are not severe, ACTOS may not be right for you.

Call your doctor right away if you have any of the following:

- swelling or fluid retention, especially in the ankles or legs.
- shortness of breath or trouble breathing, especially when you lie down.
- an unusually fast increase in weight.
- unusual tiredness.

ACTOS can have other serious side effects. See "What are the possible side effects of ACTOS?"

What is ACTOS?

ACTOS is a prescription medicine used with diet and exercise to improve blood sugar (glucose) control in adults with type 2 diabetes. ACTOS is a diabetes medicine called pioglitazone hydrochloride that may be taken alone or with other diabetes medicines.

Your doctor will decide if you should take ACTOS.

It is important to eat the right foods, lose weight if needed, and exercise regularly in order to manage your type 2 diabetes. Diet, weight loss, and exercise are the main treatments for type 2 diabetes and they also help your diabetes medicines work better for you.

ACTOS has not been studied in children and is not recommended for children under the age of 18. The risks of giving ACTOS to a child are not known. See "What are some other possible side effects of ACTOS?"

Who should not take ACTOS?

Do not take ACTOS if you:

- are allergic to any of the ingredients in ACTOS. See the end of this Medication Guide for a complete list of ingredients in ACTOS.

People with severe heart failure should not start taking ACTOS. See "What is the most important information I should know about ACTOS?"

What should I tell my doctor before taking ACTOS?

Before starting ACTOS, ask your doctor about what the choices are for diabetes medicines and what the expected benefits and possible risks are for you in particular.

Tell your doctor about all of your medical conditions, especially if you:

- have heart failure.
- have type 1 ("juvenile") diabetes or had diabetic ketoacidosis. These conditions should be treated with insulin.
- have a type of diabetic eye disease called macular edema (swelling of the back of the eye).
- have liver problems. Your doctor should do blood tests to check your liver before you start taking ACTOS and during treatment as needed.
- are pregnant or planning to become pregnant. Actos should not be used during pregnancy. It is not known if ACTOS can harm your unborn baby. Talk to your doctor about the best way to control your blood glucose levels while pregnant.
- are a premenopausal woman (before the "change of life"), who does not have periods regularly or at all. ACTOS may increase your chance of becoming pregnant. Talk to your doctor about birth control choices while taking ACTOS. Tell your doctor right away if you become pregnant while taking ACTOS.
- are breastfeeding or plan to breastfeed. It is not known if ACTOS passes into your milk and if it can harm your baby. You should not take ACTOS if you breastfeed your baby. Talk to your doctor about the best way to control your blood glucose levels while breastfeeding.

Tell your doctor about all the medicines you take including prescription and non-prescription medicines, vitamins, and herbal supplements. ACTOS and some of your other medicines can affect each other. You may need to have your dose of ACTOS or certain other medicines adjusted. Certain other medicines can affect your blood sugar (glucose) control.

Know the medicines you take. Keep a list of your medicines and show it to your doctor and pharmacist before you start a new medicine. They will tell you if it is okay to take ACTOS with other medicines.

How should I take ACTOS?

- Take ACTOS exactly as prescribed.
- Your doctor may need to change your dose of ACTOS to control your blood glucose. Do not change your dose unless told to do so by your doctor.
- ACTOS may be prescribed alone or with other diabetes medicines. This will depend on how well your blood sugar is controlled.
- Take ACTOS one time each day, with or without food.
- If you miss a dose of ACTOS, take your next dose as prescribed unless your doctor tells you differently. Do not take two doses at one time the next day.
- If you take too much ACTOS, call your doctor or poison control center right away.
- If your body is under stress, for example: due to fever, infection, trauma (such as a car accident), or surgery, the dose of your diabetes medicines may need to be changed. Call your doctor right away.
- Stay on your diet and exercise programs and test your blood sugar regularly while taking ACTOS.
- Your doctor should do blood tests before starting ACTOS and from time to time to check your liver, kidneys, and blood cells.
- Your doctor should also do regular blood tests (for example, hemoglobin A1C) to check how well your blood sugar is controlled with ACTOS.
- Your doctor should check your eyes regularly. Some people have had vision changes due to swelling in the back of the eye, called macular edema, while taking ACTOS.
- It may take 2-3 months to see the full effect on your blood sugar level.

What are other possible side effects of ACTOS?

ACTOS can cause other serious side effects including:

- Weight gain. Pioglitazone, the medicine in ACTOS can cause weight gain that may be due to fluid retention or extra body fat. Weight gain due to fluid retention can be a serious problem for people with certain conditions, including heart problems. See "What is the most important information I should know about ACTOS?".
- Liver problems. It is important for your liver to be working normally when you take ACTOS. Your doctor should do blood tests to check your liver before you start taking ACTOS and during treatment as needed. Call your doctor right away if you have unexplained symptoms such as:
  - nausea or vomiting.
  - stomach pain.
  - unusual or unexplained tiredness.
  - loss of appetite.
  - dark urine.
  - yellowing of your skin or the whites of your eyes.
- Macular edema (diabetic eye disease with swelling in the back of the eye). Tell your doctor right away if you have any changes in your vision. Your doctor should check your eyes regularly.
- Fractures (broken bones), usually in the hand, upper arm, or foot in women. Talk to your doctor for advice on how to keep your bones healthy. It is not known if ACTOS can affect the bones of children.
- Low red blood cell count (anemia).
- Low blood sugar (hypoglycemia). Lightheadedness, dizziness, shakiness, or hunger may indicate that your blood sugar is too low. This can happen if you skip meals, if you use another medicine that lowers blood sugar, or if you have certain medical problems. Call your doctor if low blood sugar levels are a problem for you.
- Ovulation (release of an egg from an ovary in a woman) leading to pregnancy. Ovulation may happen when premenopausal women who do not have regular monthly periods take ACTOS. This can increase the chance of pregnancy. See "What should I tell my doctor before taking ACTOS?".

In studies of pioglitazone (the medicine in ACTOS), bladder cancer occurred in a few more people who were taking pioglitazone than in people who were taking other diabetes medicines. There were too few cases to know if the bladder cancer was related to pioglitazone.

Other common side effects of ACTOS are:

- cold-like symptoms (respiratory tract infection),
- headache,
- sinus infection,
- muscle pain,
- tooth disorder,
- sore throat.

Tell your doctor if you have any side effect that bothers you or that does not go away. These are not all the side effects of ACTOS. For more information, ask your doctor or pharmacist.

Call your doctor for medical advice about side effects. You may report side effects to FDA at 1-800-FDA-1088.

How should I store ACTOS?

- Store ACTOS at 59° to 86°F (15° to 30°C). Keep ACTOS in the original container to protect from light.
- Keep the ACTOS bottle tightly closed and protect from getting wet (away from moisture and humidity).

Keep ACTOS and all medicines out of the reach of children.

General information about ACTOS

Medicines are sometimes prescribed for purposes other than those listed in a Medication Guide. Do not use ACTOS for a condition for which it is not prescribed. Do not give ACTOS to other people, even if they have the same symptoms you have. It may harm them.

This Medication Guide summarizes the most important information about ACTOS. If you would like more information, talk with your doctor. You can ask your doctor or pharmacist for information about ACTOS that is written for healthcare professionals. For more information, go to www.actos.com or call 1-877-825-3327.

What are the ingredients in ACTOS?

Active Ingredient: pioglitazone hydrochloride

Inactive Ingredients: lactose monohydrate, hydroxypropylcellulose, carboxymethylcellulose calcium, and magnesium stearate.

Always check to make sure that the medicine you are taking is the correct one. ACTOS tablets look like this:

- 15 mg strength tablets – white to off-white, round, convex, non-scored with "ACTOS" on one side, and "15" on the other.
- 30 mg strength tablets – white to off-white, round, flat, non-scored with "ACTOS" on one side, and "30" on the other.
- 45 mg strength tablets – white to off-white, round, flat, non-scored with "ACTOS" on one side, and "45" on the other.

ACTOS® is a registered trademark of Takeda Pharmaceutical Company Limited and used under license by Takeda Pharmaceuticals America, Inc.
All other trademarks are the property of their respective owners.

This Medication Guide has been approved by the U.S. Food and Drug Administration.

Distributed by:
Takeda Pharmaceuticals America, Inc.
Deerfield, IL 60015

© 2009 Takeda Pharmaceuticals America, Inc.

September 2009
ACT0909-R2/MG

PRINCIPAL DISPLAY PANEL - 15 mg Tablet Bottle Label

NDC 21695-147-15

15 Tablets

actos®
(pioglitazone HCl)
Tablets

15 mg

Each tablet contains pioglitazone
hydrochloride equivalent to 15 mg
pioglitazone.

Dispense with Medication Guide
available in package insert or at
www.actos.com

Takeda
Rx Only

PRINCIPAL DISPLAY PANEL - 30 mg Tablet Bottle Label

NDC 21695-148-15

15 Tablets

actos®
(pioglitazone HCl)
Tablets

30 mg

Each tablet contains pioglitazone
hydrochloride equivalent to 30 mg
pioglitazone.

Dispense with Medication Guide
available in package insert or at
www.actos.com

Takeda
Rx Only